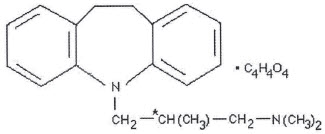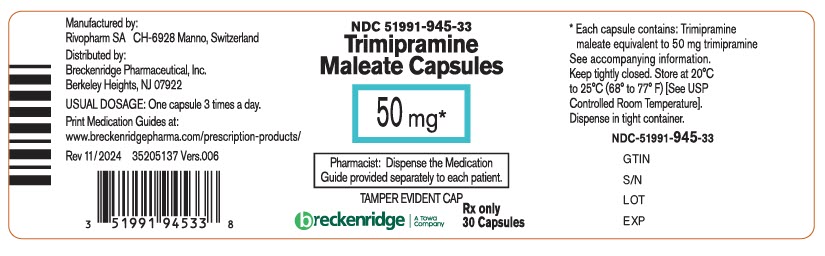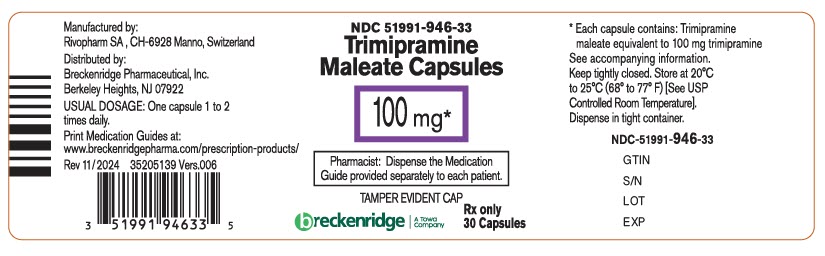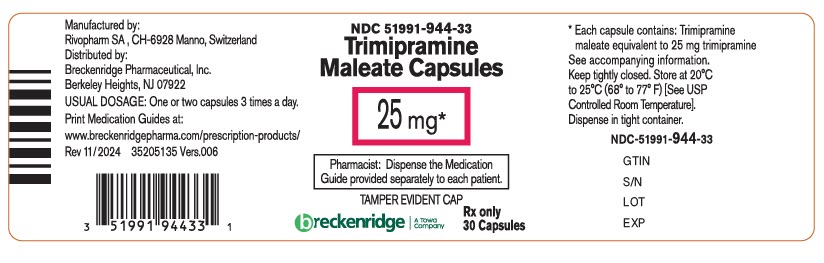 DRUG LABEL: Trimipramine Maleate
NDC: 51991-945 | Form: CAPSULE
Manufacturer: Breckenridge Pharmaceutical, Inc.
Category: prescription | Type: HUMAN PRESCRIPTION DRUG LABEL
Date: 20250714

ACTIVE INGREDIENTS: TRIMIPRAMINE MALEATE 50 mg/1 1
INACTIVE INGREDIENTS: LACTOSE MONOHYDRATE; MAGNESIUM STEARATE; GELATIN, UNSPECIFIED; TITANIUM DIOXIDE; FD&C BLUE NO. 1; FD&C YELLOW NO. 6; D&C RED NO. 28; FD&C RED NO. 40; SHELLAC; FERROSOFERRIC OXIDE; PROPYLENE GLYCOL; AMMONIA

TRIMIPRAMINE MALEATE CAPSULES

25 mg, 50 mg and 100 mg

Rx only

Suicidality and Antidepressant Drugs

Antidepressants increased the risk compared to placebo of suicidal thinking and behavior (suicidality) in children, adolescents, and young adults in short-term studies of major depressive disorder (MDD) and other psychiatric disorders. Anyone considering the use of trimipramine maleate capsules or any other antidepressant in a child, adolescent, or young adult must balance this risk with the clinical need. Short-term studies did not show an increase in the risk of suicidality with antidepressants compared to placebo in adults beyond age 24; there was a reduction in risk with antidepressants compared to placebo in adults aged 65 and older. Depression and certain other psychiatric disorders are themselves associated with increases in the risk of suicide. Patients of all ages who are started on antidepressant therapy should be monitored appropriately and observed closely for clinical worsening, suicidality, or unusual changes in behavior. Families and caregivers should be advised of the need for close observation and communication with the prescriber.

Trimipramine maleate capsules are not approved for use in pediatric patients. (See WARNINGS - Clinical Worsening and Suicide Risk, PRECAUTIONS - Information for Patients, and PRECAUTIONS - Pediatric Use)

DESCRIPTION

Trimipramine maleate is 5-(3-dimethylamino-2-methylpropyl)-10,11-dihydro-5H-dibenz (b,f) azepine acid maleate (racemic form).

Molecular Formula: C20H26N2 ∙ C4H4O4 Molecular Weight: 410.5

Trimipramine maleate capsules contain trimipramine maleate equivalent to 25 mg, 50 mg, or 100 mg of trimipramine as the base. The inactive ingredients present are lactose monohydrate and magnesium stearate. The capsule shell contains D&C Yellow 10 (25 mg), FD&C Blue 1 (25 mg, 50 mg and 100 mg), FD&C Yellow 6 (25 mg, 50 mg), D&C Red 28 (50 mg), FD&C Red 40 (50 mg), gelatin and titanium dioxide. The capsules are imprinted in black ink that contains shellac glaze, iron oxide black, propylene glycol and ammonium hydroxide.

Trimipramine maleate is prepared as a racemic mixture which can be resolved into levorotatory and dextrorotatory isomers. The asymmetric center responsible for optical isomerism is marked in the formula by an asterisk.

Trimipramine maleate is an almost odorless, white or slightly cream-colored, crystalline substance, melting at 140°-144° C. It is very slightly soluble in ether and water, is slightly soluble in ethyl alcohol and acetone, and freely soluble in chloroform and methanol at 20° C.

CLINICAL PHARMACOLOGY

Trimipramine maleate capsules are an antidepressant with an anxiety-reducing sedative component to its action. The mode of action of trimipramine maleate capsules on the central nervous system is not known. However, unlike amphetamine-type compounds it does not act primarily by stimulation of the central nervous system. It does not act by inhibition of the monoamine oxidase system.

The single-dose pharmacokinetics of trimipramine were evaluated in a comparative study of 24 elderly subjects and 24 younger subjects; no clinically relevant differences were demonstrated based on age or gender.

INDICATIONS AND USAGE

Trimipramine maleate capsules are indicated for the relief of symptoms of depression. Endogenous depression is more likely to be alleviated than other depressive states. In studies with neurotic outpatients, the drug appeared to be equivalent to amitriptyline in the less-depressed patients but somewhat less effective than amitriptyline in the more severely depressed patients. In hospitalized depressed patients, trimipramine and imipramine were equally effective in relieving depression.

CONTRAINDICATIONS

Monoamine Oxidase Inhibitors (MAOIs)

The use of MAOIs intended to treat psychiatric disorders with trimipramine maleate capsules or within 14 days of stopping treatment with trimipramine maleate capsules is contraindicated because of an increased risk of serotonin syndrome. The use of trimipramine maleate capsules within 14 days of stopping an MAOI intended to treat psychiatric disorders is also contraindicated (see WARNINGS and DOSAGE AND ADMINISTRATION).

Starting trimipramine maleate capsules in a patient who is being treated with MAOIs such as linezolid or intravenous methylene blue is also contraindicated because of an increased risk of serotonin syndrome (see WARNINGS and DOSAGE AND ADMINISTRATION).

Hypersensitivity to Tricyclic Antidepressants

Cross-sensitivity between trimipramine maleate capsules and other dibenzazepines is a possibility.

Myocardial Infarction

The drug is contraindicated during the acute recovery period after a myocardial infarction.

WARNINGS

Clinical Worsening and Suicide Risk

Patients with major depressive disorder (MDD), both adult and pediatric, may experience worsening of their depression and/or the emergence of suicidal ideation and behavior (suicidality) or unusual changes in behavior, whether or not they are taking antidepressant medications, and this risk may persist until significant remission occurs. Suicide is a known risk of depression and certain other psychiatric disorders, and these disorders themselves are the strongest predictors of suicide. There has been a long-standing concern, however, that antidepressants may have a role in inducing worsening of depression and the emergence of suicidality in certain patients during the early phases of treatment. Pooled analyses of short-term placebo-controlled trials of antidepressant drugs (SSRIs and others) showed that these drugs increase the risk of suicidal thinking and behavior (suicidality) in children, adolescents, and young adults (aged 18-24) with major depressive disorder (MDD) and other psychiatric disorders. Short-term studies did not show an increase in the risk of suicidality with antidepressants compared to placebo in adults beyond age 24; there was a reduction with antidepressants compared to placebo in adults aged 65 and older.

The pooled analysis of placebo-controlled trials in children and adolescents with MDD, obsessive compulsive disorder (OCD), or other psychiatric disorders including a total of 24 short-term trials of 9 antidepressant drugs in over 4400 patients. The pooled analyses of placebo-controlled trials in adults with MDD or other psychiatric disorders included a total of 295 short-term trials (median duration of 2 months) of 11 antidepressant drugs in over 77,000 patients. There was considerable variation in risk of suicidality among drugs, but a tendency toward an increase in the younger patients for almost all drugs studied. There were differences in absolute risk of suicidality across the different indications, with the highest incidence in MDD. The risk differences (drug vs placebo), however, were relatively stable with age strada and across indications. These risk differences (drug-placebo difference in the number of cases of suicidality per 1000 patients treated) are provided in Table 1.

Table 1
Age Range | Drug-Placebo Difference in Number of Cases of Suicidality per 1000 Patients Treated
 | Increases Compared to Placebo
< 18 | 14 additional cases
18-24 | 5 additional cases
 | Decreases Compared to Placebo
25-64 | 1 fewer case
≥ 65 | 6 fewer cases

No suicides occurred in any of the pediatric trials. There were suicides in the adult trials, but the number was not sufficient to reach any conclusion about drug effect on suicide.

It is unknown whether the suicidality risk extends to longer-term use, i.e., beyond several months. However, there is substantial evidence from placebo-controlled maintenance trials in adults with depression that the use of antidepressants can delay the recurrence of depression.

All patients being treated with antidepressants for any indication should be monitored appropriately and observed closely for clinical worsening, suicidality, and unusual changes in behavior, especially during the initial few months of a course of drug therapy, or at times of dose changes, either increases or decreases.

The following symptoms, anxiety, agitation, panic attacks, insomnia, irritability, hostility, aggressiveness, impulsivity, akathisia (psychomotor restlessness), hypomania, and mania, have been reported in adult and pediatric patients being treated with antidepressants for major depressive disorder as well as for other indications, both psychiatric and nonpsychiatric. Although a causal link between the emergence of such symptoms and either the worsening of depression and/or the emergence of suicidal impulses has not been established, there is concern that such symptoms may represent precursors to emerging suicidality.

Consideration should be given to changing the therapeutic regimen, including possibly discontinuing the medication, in patients whose depression is persistently worse, or who are experiencing emergent suicidality or symptoms that might be precursors to worsening depression or suicidality, especially if these symptoms are severe, abrupt in onset, or were not part of the patient's presenting symptoms.

Families and caregivers of patients being treated with antidepressants for major depressive disorder or other indications, both psychiatric and non-psychiatric, should be alerted about the need to monitor patients for the emergence of agitation, irritability, unusual changes in behavior, and the other symptoms described above, as well as the emergence of suicidality, and to report such symptoms immediately to health care providers. Such monitoring should include daily observation by families and caregivers. Prescriptions for trimipramine maleate capsules should be written for the smallest quantity of capsules consistent with good patient management, in order to reduce the risk of overdose.

Screening Patients for Bipolar Disorder

A major depressive episode may be the initial presentation of bipolar disorder. It is generally believed (though not established in controlled trials) that treating such an episode with an antidepressant alone may increase the likelihood of precipitation of a mixed/manic episode in patients at risk for bipolar disorder. Whether any of the symptoms described above represent such a conversion is unknown. However, prior to initiating treatment with an antidepressant, patients with depression symptoms should be adequately screened to determine if they are at risk for bipolar disorder; such screening should include a detailed psychiatric history, including a family history of suicide, bipolar disorder, and depression. It should be noted that trimipramine maleate capsules are not approved for use in treating bipolar depression.

Serotonin Syndrome

The development of a potentially life-threatening serotonin syndrome has been reported with SNRIs and SSRIs, including trimipramine maleate capsules, alone, but particularly with concomitant use of other serotonergic drugs (including triptans, tricyclic antidepressants, fentanyl, lithium, tramadol, tryptophan, buspirone, and St. John's wort) and with drugs that impair metabolism of serotonin (in particular, MAOIs, both those intended to treat psychiatric disorders and also others, such as linezolid and intravenous methylene blue).

Serotonin syndrome symptoms may include mental status changes (e.g., agitation, hallucinations, delirium, and coma), autonomic instability (e.g., tachycardia, labile blood pressure, dizziness, diaphoresis, flushing, hyperthermia), neuromuscular symptoms (e.g., tremor, rigidity, myoclonus, hyperreflexia, incoordination), seizures, and/or gastrointestinal symptoms (e.g., nausea, vomiting, diarrhea). Patients should be monitored for the emergence of serotonin syndrome.

The concomitant use of trimipramine maleate capsules with MAOIs intended to treat psychiatric disorders is contraindicated. Trimipramine maleate capsules should also not be started in a patient who is being treated with MAOIs such as linezolid or intravenous methylene blue. All reports with methylene blue that provided information on the route of administration involved intravenous administration in the dose range of 1 mg/kg to 8 mg/kg. No reports involved the administration of methylene blue by other routes (such as oral tablets or local tissue injection) or at lower doses. There may be circumstances when it is necessary to initiate treatment with an MAOI such as linezolid or intravenous methylene blue in a patient taking trimipramine maleate capsules. Trimipramine maleate capsules should be discontinued before initiating treatment with the MAOI (see CONTRAINDICATIONS and DOSAGE AND ADMINISTRATION).

If concomitant use of trimipramine maleate capsules with other serotonergic drugs, including triptans, tricyclic antidepressants, fentanyl, lithium, tramadol, buspirone, tryptophan, and St. John's wort is clinically warranted, patients should be made aware of a potential increased risk for serotonin syndrome, particularly during treatment initiation and dose increases.

Treatment with trimipramine maleate capsules and any concomitant serotonergic agents should be discontinued immediately if the above events occur and supportive symptomatic treatment should be initiated.

Angle-Closure Glaucoma

The pupillary dilation that occurs following use of many antidepressant drugs including trimipramine maleate capsules may trigger an angle closure attack in a patient with anatomically narrow angles who does not have a patent iridectomy.

General Consideration for Use

Extreme caution should be used when this drug is given to patients with any evidence of cardiovascular disease because of the possibility of conduction defects, arrhythmias, myocardial infarction, strokes, and tachycardia. Caution is advised in patients with history of urinary retention because of the drug's anticholinergic properties; hyperthyroid patients or those on thyroid medication because of the possibility of cardiovascular toxicity; patients with a history of seizure disorder, because this drug has been shown to lower the seizure threshold; patients receiving guanethidine or similar agents, since trimipramine maleate capsules (trimipramine maleate) may block the pharmacologic effects of these drugs.

Since the drug may impair the mental and/or physical abilities required for the performance of potentially hazardous tasks, such as operating an automobile or machinery, the patient should be cautioned accordingly.

PRECAUTIONS

General

The possibility of suicide is inherent in any severely depressed patient and persists until a significant remission occurs. When a patient with a serious suicidal potential is not hospitalized, the prescription should be for the smallest amount feasible.

In schizophrenic patients activation of the psychosis may occur and require reduction of dosage or the addition of a major tranquilizer to the therapeutic regimen.

Manic or hypomanic episodes may occur in some patients, in particular those with cyclic-type disorders. In some cases therapy with trimipramine maleate capsules must be discontinued until the episode is relieved, after which therapy may be reinstituted at lower dosages if still required.

Concurrent administration of trimipramine maleate capsules and electroshock therapy may increase the hazards of therapy. Such treatment should be limited to those patients for whom it is essential. When possible, discontinue the drug for several days prior to elective surgery.

Trimipramine maleate capsules should be used with caution in patients with impaired liver function.

Chronic animal studies showed occasional occurrence of hepatic congestion, fatty infiltration, or increased serum liver enzymes at the highest dose of 60 mg/kg/day.

Both elevation and lowering of blood sugar have been reported with tricyclic antidepressants.

Information for Patients

Prescribers or other health professionals should inform patients, their families, and their caregivers about the benefits and risks associated with treatment with trimipramine maleate capsules and should counsel them in its appropriate use. A patient Medication Guide about "Antidepressant Medicines, Depression and other Serious Mental Illness, and Suicidal Thoughts or Actions" is available for trimipramine maleate capsules. The prescriber or health professional should instruct patients, their families, and their caregivers to read the Medication Guide and should assist them in understanding its contents. Patients should be given the opportunity to discuss the contents of the Medication Guide and to obtain answers to any questions they may have. The complete text of the Medication Guide is reprinted at the end of this document.

Patients should be advised of the following issues and asked to alert their prescriber if these occur while taking trimipramine maleate capsules.

Clinical Worsening and Suicide Risk

Patients, their families, and their caregivers should be encouraged to be alert to the emergence of anxiety, agitation, panic attacks, insomnia, irritability, hostility, aggressiveness, impulsivity, akathisia (psychomotor restlessness), hypomania, mania, other unusual changes in behavior, worsening of depression, and suicidal ideation, especially early during antidepressant treatment and when the dose is adjusted up or down. Families and caregivers of patients should be advised to look for the emergence of such symptoms on a day-to-day basis, since changes may be abrupt. Such symptoms should be reported to the patient's prescriber or health professional, especially if they are severe, abrupt in onset, or were not part of the patient's presenting symptoms. Symptoms such as these may be associated with an increased risk for suicidal thinking and behavior and indicate a need for very close monitoring and possibly changes in the medication.

Patients should be advised that taking trimipramine maleate capsules can cause mild pupillary dilation, which in susceptible individuals, can lead to an episode of angle closure glaucoma. Pre-existing glaucoma is almost always open-angle glaucoma because angle closure glaucoma, when diagnosed, can be treated definitively with iridectomy. Open-angle glaucoma is not a risk factor for angle closure glaucoma. Patients may wish to be examined to determine whether they are susceptible to angle closure, and have a prophylactic procedure (e.g., iridectomy), if they are susceptible.

Drug Interactions

Cimetidine

There is evidence that cimetidine inhibits the elimination of tricyclic antidepressants. Downward adjustment of trimipramine maleate capsules dosage may be required if cimetidine therapy is initiated; upward adjustment if cimetidine therapy is discontinued.

Alcohol

Patients should be warned that the concomitant use of alcoholic beverages may be associated with exaggerated effects.

Catecholamines/Anticholinergics

It has been reported that tricyclic antidepressants can potentiate the effects of catecholamines. Similarly, atropine-like effects may be more pronounced in patients receiving anticholinergic therapy. Therefore, particular care should be exercised when it is necessary to administer tricyclic antidepressants with sympathomimetic amines, local decongestants, local anesthetics containing epinephrine, atropine or drugs with an anticholinergic effect. In resistant cases of depression in adults, a dose of 2.5 mg/kg/day may have to be exceeded. If a higher dose is needed, ECG monitoring should be maintained during the initiation of therapy and at appropriate intervals during stabilization of dose.

Drugs Metabolized by P450 2D6

The biochemical activity of the drug metabolizing isozyme cytochrome P450 2D6 (debrisoquin hydroxylase) is reduced in a subset of the caucasian population (about 7-10% of caucasians are so called "poor metabolizers"); reliable estimates of the prevalence of reduced P450 2D6 isozyme activity among Asian, African, and other populations are not yet available. Poor metabolizers have higher than expected plasma concentrations of tricyclic antidepressants (TCAs) when given usual doses. Depending on the fraction of drug metabolized by P450 2D6, the increase in plasma concentration may be small, or quite large (8 fold increase in plasma AUC of the TCA).

In addition, certain drugs inhibit the activity of the isozyme and make normal metabolizers resemble poor metabolizers. An individual who is stable on a given dose of TCA may become abruptly toxic when given one of these inhibiting drugs as concomitant therapy. The drugs that inhibit cytochrome P450 2D6 include some that are not metabolized by the enzyme (quinidine; cimetidine) and many that are substrates for P450 2D6 (many other antidepressants, phenothiazines, and the Type 1C antiarrhythmics propafenone and flecainide). While all the selective serotonin reuptake inhibitors (SSRIs), e.g., fluoxetine, sertraline, and paroxetine, inhibit P450 2D6, they may vary in the extent of inhibition. The extent to which SSRI TCA interactions may pose clinical problems will depend on the degree of inhibition and the pharmacokinetics of the SSRI involved. Nevertheless, caution is indicated in the co-administration of TCAs with any of the SSRIs and also in switching from one class to the other. Of particular importance, sufficient time must elapse before initiating TCA treatment in a patient being withdrawn from fluoxetine, given the long half-life of the parent and active metabolite (at least 5 weeks may be necessary).

Concomitant use of tricyclic antidepressants with drugs that can inhibit cytochrome P450 2D6 may require lower doses than usually prescribed for either the tricyclic antidepressant or the other drug. Furthermore, whenever one of these other drugs is withdrawn from co-therapy, an increased dose of tricyclic antidepressant may be required. It is desirable to monitor TCA plasma levels whenever a TCA is going to be co-administered with another drug known to be an inhibitor of P450 2D6.

Monoamine Oxidase Inhibitors (MAOIs)

(See CONTRAINDICATIONS, WARNINGS, and DOSAGE AND ADMINISTRATION.)

Serotonergic Drugs

(See CONTRAINDICATIONS, WARNINGS, and DOSAGE AND ADMINISTRATION.)

Carcinogenesis, Mutagenesis, Impairment of Fertility

Semen studies in man (four schizophrenics and nine normal volunteers) revealed no significant changes in sperm morphology. It is recognized that drugs having a parasympathetic effect, including tricyclic antidepressants, may alter the ejaculatory response.

Chronic animal studies showed occasional evidence of degeneration of seminiferous tubules at the highest dose of 60 mg/kg/day.

Pregnancy

Teratogenic Effects

Pregnancy Category C

Trimipramine maleate capsules have shown evidence of embryotoxicity and/or increased incidence of major anomalies in rats or rabbits at doses 20 times the human dose. There are no adequate and well-controlled studies in pregnant women. Trimipramine maleate capsules should be used during pregnancy only if the potential benefit justifies the potential risk to the fetus.

Pediatric Use

Safety and effectiveness in the pediatric population have not been established (see BOXED WARNING and WARNINGS -Clinical Worsening and Suicide Risk). Anyone considering the use of trimipramine maleate capsules in a child or adolescent must balance the potential risks with the clinical need.

Geriatric Use

Clinical studies of trimipramine maleate capsules (trimipramine maleate) were not adequate to determine whether subjects aged 65 and over respond differently from younger subjects.

The pharmacokinetics of trimipramine were not substantially altered in the elderly (see CLINICAL PHARMACOLOGY).

Trimipramine maleate capsules are known to be substantially excreted by the kidney. Clinical circumstances, some of which may be more common in the elderly, such as hepatic or renal impairment, should be considered (see PRECAUTIONS -General).

Greater sensitivity (e.g., confusional states, sedation) of some older individuals cannot be ruled out (see ADVERSE REACTIONS). In general, dose selection for an elderly patient should be cautious, usually starting at a lower dose (see DOSAGE AND ADMINISTRATION).

ADVERSE REACTIONS

Note: The pharmacological similarities among the tricyclic antidepressants require that each of the reactions be considered when trimipramine maleate capsules are administered. Some of the adverse reactions included in this listing have not in fact been reported with trimipramine maleate capsules.

Cardiovascular

Hypotension, hypertension, tachycardia, palpitation, myocardial infarction, arrhythmias, heart block, stroke.

Psychiatric

Confusional states (especially the elderly) with hallucinations, disorientation, delusions; anxiety, restlessness, agitation; insomnia and nightmares; hypomania; exacerbation of psychosis.

Neurological

Numbness, tingling, paresthesias of extremities; incoordination, ataxia, tremors; peripheral neuropathy; extrapyramidal symptoms; seizures, alterations in EEG patterns; tinnitus; syndrome of inappropriate ADH (antidiuretic hormone) secretion.

Anticholinergic

Dry mouth and, rarely, associated sublingual adenitis; blurred vision, disturbances of accommodation, mydriasis, constipation, paralytic ileus; urinary retention, delayed micturition, dilation of the urinary tract.

Allergic

Skin rash, petechiae, urticaria, itching, photosensitization, edema of face and tongue.

Hematologic

Bone marrow depression including agranulocytosis, eosinophilia; purpura; thrombocytopenia. Leukocyte and differential counts should be performed in any patient who develops fever and sore throat during therapy; the drug should be discontinued if there is evidence of pathological neutrophil depression.

Gastrointestinal

Nausea and vomiting, anorexia, epigastric distress, diarrhea, peculiar taste, stomatitis, abdominal cramps, black tongue.

Endocrine

Gynecomastia in the male; breast enlargement and galactorrhea in the female; increased or decreased libido, impotence; testicular swelling; elevation or depression of blood sugar levels.

Other

Jaundice (simulating obstructive); altered liver function; weight gain or loss; perspiration; flushing; urinary frequency; drowsiness, dizziness, weakness, and fatigue; headache; parotid swelling; alopecia.

Withdrawal Symptoms

Though not indicative of addiction, abrupt cessation of treatment after prolonged therapy may produce nausea, headache, and malaise.

DOSAGE AND ADMINISTRATION

Dosage should be initiated at a low level and increased gradually, noting carefully the clinical response and any evidence of intolerance.

Lower dosages are recommended for elderly patients and adolescents. Lower dosages are also recommended for outpatients as compared to hospitalized patients who will be under close supervision. It is not possible to prescribe a single dosage schedule of trimipramine maleate capsules that will be therapeutically effective in all patients. The physical psychodynamic factors contributing to depressive symptomatology are very complex; spontaneous remissions or exacerbations of depressive symptoms may occur with or without drug therapy. Consequently, the recommended dosage regimens are furnished as a guide which may be modified by factors such as the age of the patient, chronicity and severity of the disease, medical condition of the patient, and degree of psychotherapeutic support.

Most antidepressant drugs have a lag period of ten days to four weeks before a therapeutic response is noted. Increasing the dose will not shorten this period but rather increase the incidence of adverse reactions.

Usual Adult Dose

Outpatients and Office Patients

Initially, 75 mg/day in divided doses, increased to 150 mg/day. Dosages over 200 mg/day are not recommended. Maintenance therapy is in the range of 50 to 150 mg/day. For convenient therapy and to facilitate patient compliance, the total dosage requirement may be given at bedtime.

Hospitalized Patients

Initially, 100 mg/day in divided doses. This may be increased gradually in a few days to 200 mg/day, depending upon individual response and tolerance. If improvement does not occur in 2 to 3 weeks, the dose may be increased to the maximum recommended dose of 250 to 300 mg/day.

Adolescent and Geriatric Patients

Initially, a dose of 50 mg/day is recommended, with gradual increments up to 100 mg/day, depending upon patient response and tolerance.

Maintenance

Following remission, maintenance medication may be required for a longer period of time, at the lowest dose that will maintain remission. Maintenance therapy is preferably administered as a single dose at bedtime. To minimize relapse, maintenance therapy should be continued for about three months.

Switching a Patient To or From a Monoamine Oxidase Inhibitor (MAOI) Intended to Treat Psychiatric Disorders

At least 14 days should elapse between discontinuation of an MAOI intended to treat psychiatric disorders and initiation of therapy with trimipramine maleate capsules. Conversely, at least 14 days should be allowed after stopping trimipramine maleate capsules before starting an MAOI intended to treat psychiatric disorders (see CONTRAINDICATIONS).

Use of Trimipramine Maleate Capsules With Other MAOIs, Such as Linezolid or Methylene Blue

Do not start trimipramine maleate capsules in a patient who is being treated with linezolid or intravenous methylene blue because there is increased risk of serotonin syndrome. In a patient who requires more urgent treatment of a psychiatric condition, other interventions, including hospitalization, should be considered (see CONTRAINDICATIONS).

In some cases, a patient already receiving therapy with trimipramine maleate capsules may require urgent treatment with linezolid or intravenous methylene blue. If acceptable alternatives to linezolid or intravenous methylene blue treatment are not available and the potential benefits of linezolid or intravenous methylene blue treatment are judged to outweigh the risks of serotonin syndrome in a particular patient, trimipramine maleate capsules should be stopped promptly, and linezolid or intravenous methylene blue can be administered. The patient should be monitored for symptoms of serotonin syndrome for 2 weeks or until 24 hours after the last dose of linezolid or intravenous methylene blue, whichever comes first. Therapy with trimipramine maleate capsules may be resumed 24 hours after the last dose of linezolid or intravenous methylene blue (see WARNINGS).

The risk of administering methylene blue by non-intravenous routes (such as oral tablets or by local injection) or in intravenous doses much lower than 1 mg/kg with trimipramine maleate capsules is unclear. The clinician should, nevertheless, be aware of the possibility of emergent symptoms of serotonin syndrome with such use (see WARNINGS).

OVERDOSAGE [Poisindex® Toxicologic Management. Topic: Antidepressants, Tricyclic Micromedex Inc. Vol. 85.]

Deaths may occur from overdosage with this class of drugs. Multiple drug ingestion (including alcohol) is common in deliberate tricyclic antidepressant overdose. As the management is complex and changing, it is recommended that the physician contact a poison control center for current information on treatment. Signs and symptoms of toxicity develop rapidly after tricyclic antidepressant overdose, therefore, hospital monitoring is required as soon as possible.

Manifestations

Critical manifestations of overdose include: cardiac dysrhythmias, severe hypotension, convulsions, and CNS depression, including coma. Changes in the electrocardiogram, particularly in QRS axis or width, are clinically significant indicators of tricyclic antidepressant toxicity.

Other signs of overdose may include: confusion, disturbed concentration, transient visual hallucinations, dilated pupils, agitation, hyperactive reflexes, stupor, drowsiness, muscle rigidity, vomiting, hypothermia, hyperpyrexia, or any of the symptoms listed under ADVERSE REACTIONS.

Management

General

Obtain an ECG and immediately initiate cardiac monitoring. Protect the patient's airway, establish an intravenous line and initiate gastric decontamination. A minimum of six hours of observation with cardiac monitoring and observation for signs of CNS or respiratory depression, hypotension, cardiac dysrhythmias and/or conduction blocks, and seizures is necessary. If signs of toxicity occur at any time during this period, extended monitoring is required. There are case reports of patients succumbing to fatal dysrhythmias late after overdose; these patients had clinical evidence of significant poisoning prior to death and most received inadequate gastrointestinal decontamination. Plasma drug levels may not reflect the severity of the poisoning. Therefore, monitoring of plasma drug levels alone should not guide management of the patient.

Gastrointestinal Decontamination

All patients suspected of tricyclic antidepressant overdose should receive gastrointestinal decontamination. This should include large volume gastric lavage followed by activated charcoal. If consciousness is impaired, the airway should be secured prior to lavage. Emesis is contraindicated.

Cardiovascular

A maximal limb-lead QRS duration of ≥ 0.10 seconds has been associated with an increased incidence of seizures. A QRS duration of ≥ 0.16 seconds has been associated with an increased incidence of ventricular dysrhythmias. Intravenous sodium bicarbonate should be used to maintain the serum pH in the range of 7.45 to 7.55. If the pH response is inadequate, hyperventilation may also be used. Concomitant use of hyperventilation and sodium bicarbonate should be done with extreme caution, with frequent pH monitoring. A pH > 7.60 or a pCO2 < 20 mm Hg is undesirable. Dysrhythmias unresponsive to sodium bicarbonate therapy/hyperventilation may respond to lidocaine, bretylium or phenytoin. Type 1A and 1C antiarrhythmics are generally contraindicated (e.g., quinidine, disopyramide, and procainamide).

In rare instances, hemoperfusion may be beneficial in acute refractory cardiovascular instability in patients with acute toxicity. However, hemodialysis, peritoneal dialysis, exchange transfusions, and forced diuresis generally have been reported as ineffective in tricyclic antidepressant poisoning.

CNS

In patients with CNS depression, early intubation is advised because of the potential for abrupt deterioration. Seizures should be controlled with benzodiazepines, or if these are ineffective, other anticonvulsants (e.g., phenobarbital, phenytoin). Physostigmine is not recommended except to treat life-threatening symptoms that have been unresponsive to other therapies, and then only in consultation with a poison control center.

Psychiatric Follow-up

Since overdosage is often deliberate, patients may attempt suicide by other means during the recovery phase. Psychiatric referral may be appropriate.

Pediatric Management

The principles of management of child and adult overdosages are similar. It is strongly recommended that the physician contact the local poison control center for specific pediatric treatment.

HOW SUPPLIED

Trimipramine Maleate Capsules

25 mg - #3 | Capsules, with a yellow opaque body and blue opaque cap in bottles of 100 (NDC 51991-944-01) and in bottles of 30 (NDC 51991-944-33). Capsules contain white or almost white powder. Printed with TR25 in black ink on the cap.
50 mg - #2 | Capsules, with an orange opaque body and blue opaque cap in bottles of 100 (NDC 51991-945-01)and in bottles of 30 (NDC 51991-945-33). Capsules contain white or almost white powder. Printed with TR50 in black ink on the cap.
100 mg - #0 | Capsules, with a white opaque body and light blue opaque cap in bottles of 100 (NDC 51991-946-01) and in bottles of 30 (NDC 51991-946-33). Capsules contain white or almost white powder. Printed with TR100 in black ink on the cap.

STORAGE AND HANDLING

Store at 20°-25°C (68°-77°F) [See USP Controlled Room Temperature].

Keep bottles tightly closed.

Dispense in a tight container.

Dispense with Medication Guide available at: www.breckenridgepharma.com/prescription-products/

Distributed by:
Breckenridge Pharmaceutical, Inc.
Berkeley Heights, NJ 07922

Manufactured by:
Rivopharm SA
6928, Manno, Switzerland

To report SUSPECTED ADVERSE REACTIONS, contact Breckenridge Pharmaceutical, Inc. at 1-800-367-3395, or FDA at 1-800-FDA-1088 or www.fda.gov/medwatch.

Revised: october 2024

Medication Guide Trimipramine Maleate (trye-MIP-ra-meen MAL-ee-ate) Capsules

Antidepressant Medicines, Depression and other Serious Mental Illnesses, and Suicidal Thoughts or Actions

Dispense with Medication Guide available at: www.breckenridgepharma.com/prescription-products/

Read the Medication Guide that comes with you or your family member's antidepressant medicine. This Medication Guide is only about the risk of suicidal thoughts and actions with antidepressant medicines. Talk to your, or your family member's, healthcare provider about:

- all risks and benefits of treatment with antidepressant medicines
- all treatment choices for depression or other serious mental illness

What is the most important information I should know about antidepressant medicines, depression and other serious mental illnesses, and suicidal thoughts or actions?

1. Antidepressant medicines may increase suicidal thoughts or actions in some children, teenagers, and young adults within the first few months of treatment.

2. Depression and other serious mental illnesses are the most important causes of suicidal thoughts and actions. Some people may have a particularly high risk of having suicidal thoughts or actions. These include people who have (or have a family history of) bipolar illness (also called manic-depressive illness) or suicidal thoughts or actions.

3. How can I watch for and try to prevent suicidal thoughts and actions in myself or a family member?

- Pay close attention to any changes, especially sudden changes, in mood, behaviors, thoughts, or feelings. This is very important when an antidepressant medicine is started or when the dose is changed.
- Call the healthcare provider right away to report new or sudden changes in mood, behavior, thoughts, or feelings.
- Keep all follow-up visits with the healthcare provider as scheduled. Call the healthcare provider between visits as needed, especially if you have concerns about symptoms.

Call a healthcare provider right away if you or your family member has any of the following symptoms, especially if they are new, worse, or worry you:

- thoughts about suicide or dying
- attempts to commit suicide
- new or worse depression
- new or worse anxiety
- feeling very agitated or restless
- panic attacks
- trouble sleeping (insomnia)
- new or worse irritability
- acting aggressive, being angry, or violent
- acting on dangerous impulses
- an extreme increase in activity and talking (mania)
- other unusual changes in behavior or mood

Visual Problems

- eye pain
- changes in vision
- swelling or redness in or around the eye

Only some people are at risk for these problems. You may want to undergo an eye examination to see if you are at risk and receive preventative treatment if you are.

Who should not take trimipramine maleate capsules?

- Do not take trimipramine maleate capsules if you take a monoamine oxidase inhibitor (MAOI). Ask your healthcare provider or pharmacist if you are not sure if you take an MAOI, including the antibiotic linezolid.
- Do not take an MAOI within 2 weeks of stopping trimipramine maleate capsules unless directed to do so by your physician.
- Do not start trimipramine maleate capsules if you stopped taking an MAOI in the last 2 weeks unless directed to do so by your physician.

What else do I need to know about antidepressant medicines?

- Never stop an antidepressant medicine without first talking to a healthcare provider. Stopping an antidepressant medicine suddenly can cause other symptoms.
- Antidepressants are medicines used to treat depression and other illnesses. It is important to discuss all the risks of treating depression and also the risks of not treating it. Patients and their families or other caregivers should discuss all treatment choices with the healthcare provider, not just the use of antidepressants.
- Antidepressant medicines have other side effects. Talk to the healthcare provider about the side effects of the medicine prescribed for you or your family member.
- Antidepressant medicines can interact with other medicines. Know all of the medicines that you or your family member takes. Keep a list of all medicines to show the healthcare provider. Do not start new medicines without first checking with your healthcare provider.
- Not all antidepressant medicines prescribed for children are FDA approved for use in children. Talk to your child's healthcare provider for more information.

This Medication Guide has been approved by the U.S. Food and Drug Administration.

Call your doctor for medical advice about side effects. You may report side effects to FDA at 1-800-FDA-1088.

Revised: october 2024

Distributed by:
Breckenridge Pharmaceutical, Inc.
Berkeley Heights, NJ 07922

Manufactured by:
Rivopharm SA
6928, Manno, Switzerland

PRINCIPAL DISPLAY PANEL - 50 mg Capsule Bottle Label

NDC 51991-945-33

Trimipramine
Maleate Capsules

50 mg*

Pharmacist: Dispense the Medication
Guide provided separately to each patient.

TAMPER EVIDENT CAP

breckenridge
A Towa
Company

Rx only
30 Capsules

PRINCIPAL DISPLAY PANEL - 100 mg Capsule Bottle Label

NDC 51991-946-33

Trimipramine
Maleate Capsules

100 mg*

Pharmacist: Dispense the Medication
Guide provided separately to each patient.

TAMPER EVIDENT CAP

breckenridge
A Towa
Company

Rx only
30 Capsules

PRINCIPAL DISPLAY PANEL - 25 mg Capsule Bottle Label

NDC 51991-944-33

Trimipramine
Maleate Capsules

25 mg*

Pharmacist: Dispense the Medication
Guide provided separately to each patient.

TAMPER EVIDENT CAP

breckenridge
A Towa
Company

Rx only
30 Capsules